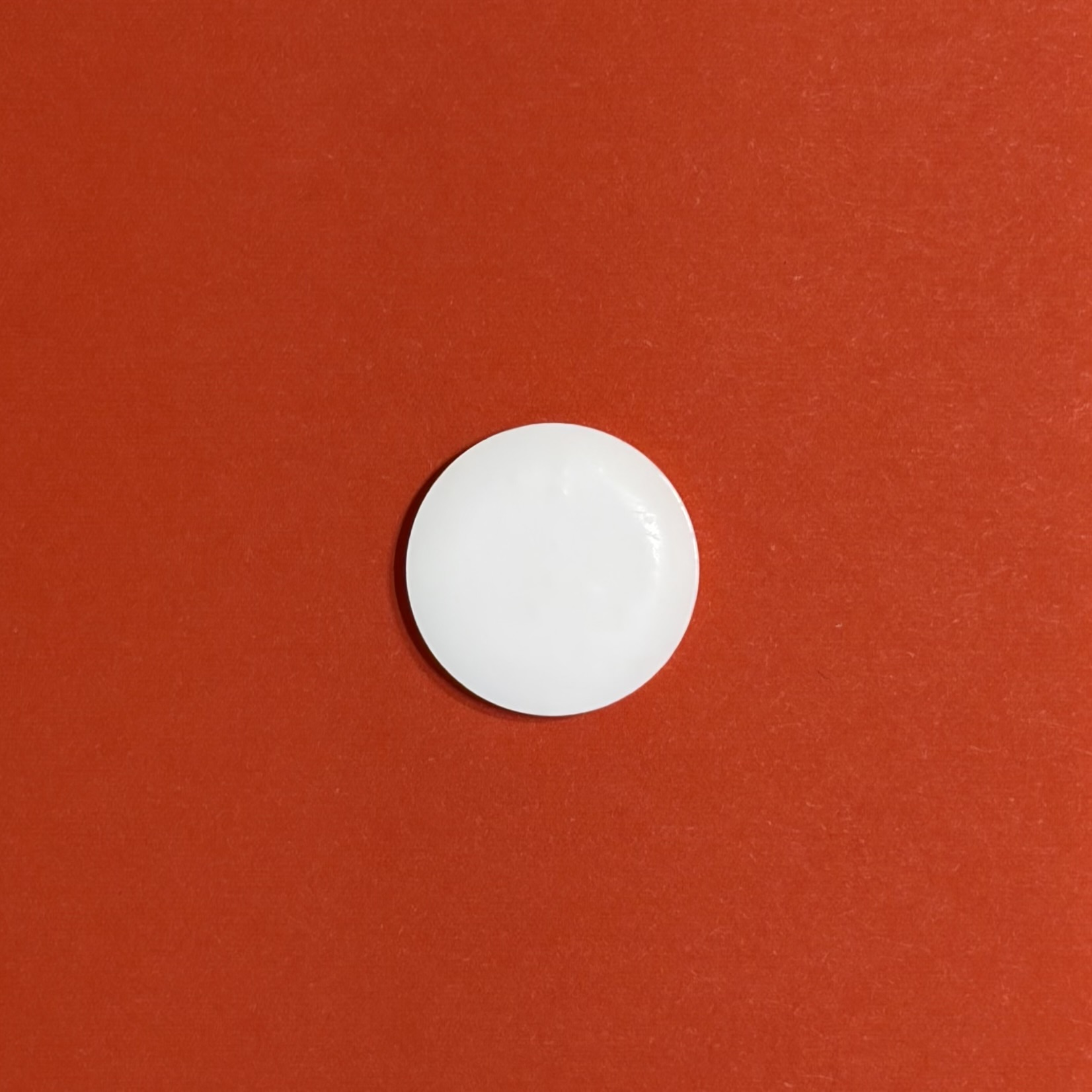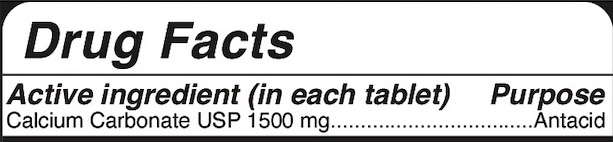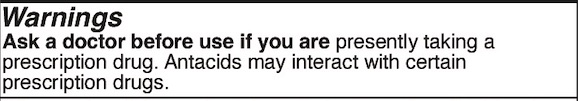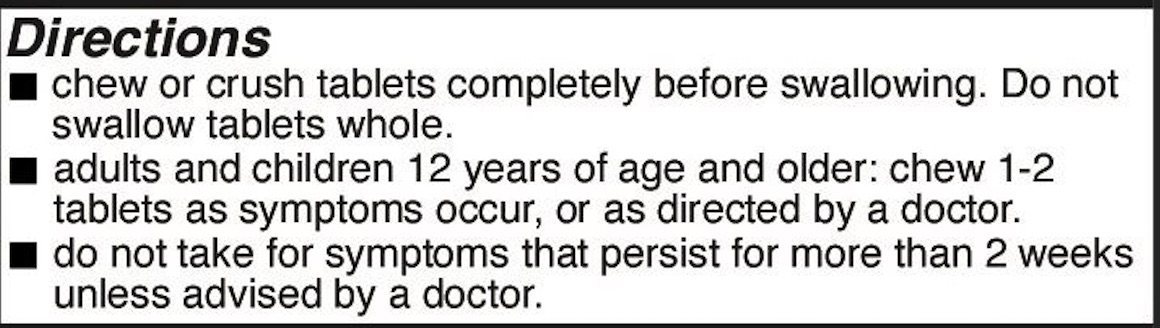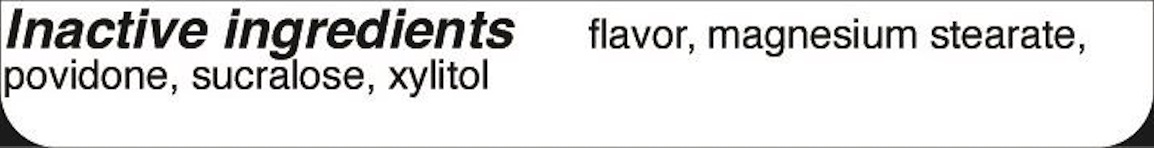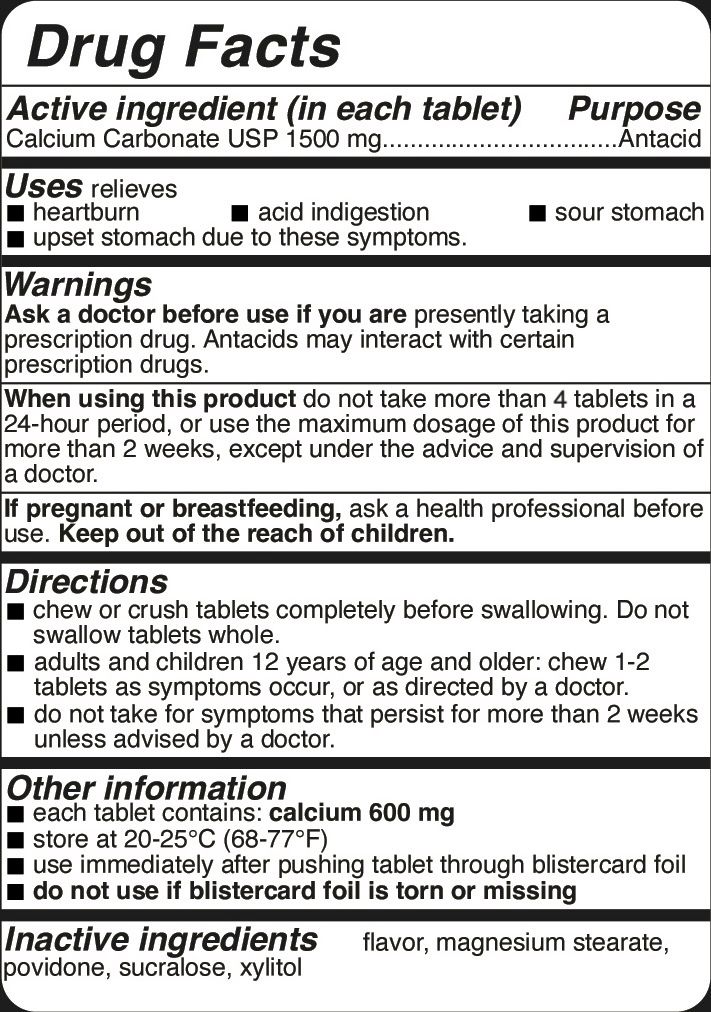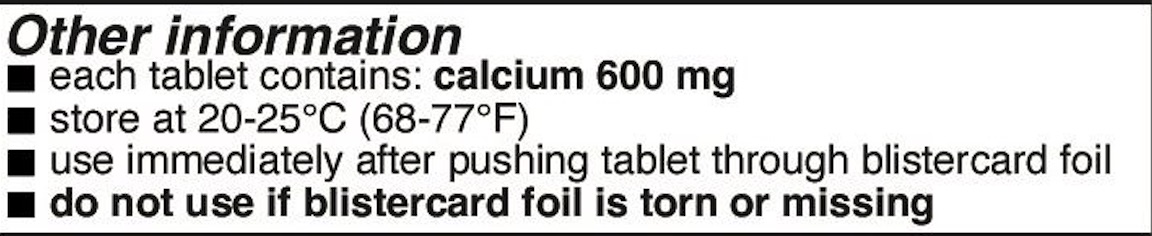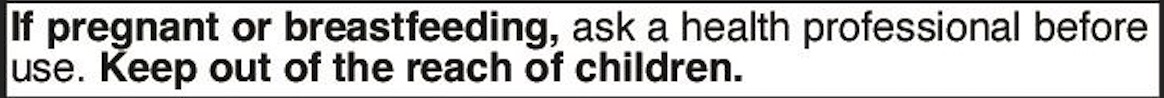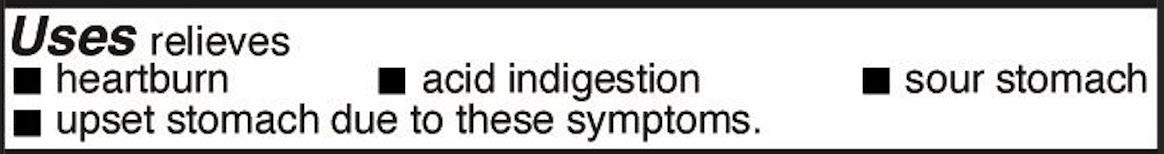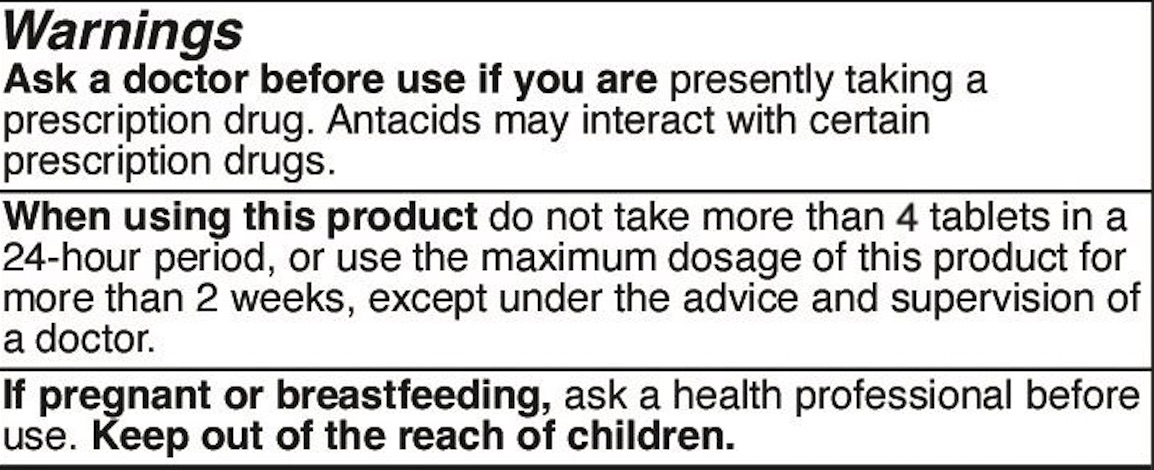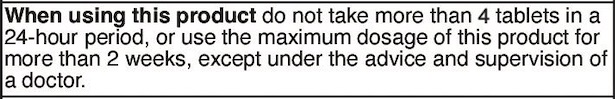 DRUG LABEL: Nova Antacid
NDC: 87355-100 | Form: TABLET, CHEWABLE
Manufacturer: Blueberri Inc.
Category: otc | Type: HUMAN OTC DRUG LABEL
Date: 20260302

ACTIVE INGREDIENTS: CALCIUM CARBONATE 1500 mg/1 1
INACTIVE INGREDIENTS: POVIDONE K30; XYLITOL; SUCRALOSE; MAGNESIUM STEARATE

Active ingredient (in each tablet)

Calcium Carbonate USP 1500 mg

Purpose

Antacid

Uses

Uses relieves

- heartburn
- acid indigestion
- sour stomach
- upset stomach due to these symptoms.

Warnings

Warnings - Ask Doctor Section

Ask a doctor before use if you are presently taking a prescription drug. Antacids may interact with certain prescription drugs.

When using section

When using this product do not take more than 4 tablets in a 24-hour period, or use the maximum dosage of this product for more than 2 weeks, except under the advice and supervision of a doctor.

Pregnancy or breast feeding section

If pregnant or breastfeeding, ask a health care professional before use.

Keep out of reach of children section

Keep out of the reach of children.

Directions

- chew or crush tablets completely before swallowing. Do not swallow tablets whole.
- adults and children 12 years of age and older: chew 1-2 tablets as symptoms occur, or as directed by a doctor.
- do not take for symptoms that persist for more than 2 weeks unless advised by a doctor.

Other information

- each tablet contains: calcium 600 mg
- store at 20-25°C (68-77°F)
- use immediately after pushing tablet through blistercard foil
- do not use if blistercard foil is torn or missing

Inactive ingredients

flavor, magnesium stearate, povidone, sucralose, xylitol

Questions or comments?

Email hello@shopmilky.com

Nova Antacid (PDP Artwork to be finalized prior to marketing start date)

Nova Antacid

1500mg calcium carbonate per tablet

Strawberry-Watermelon Flavor

Sugar Free

Contains 64 chewable tablets

Drug Facts: